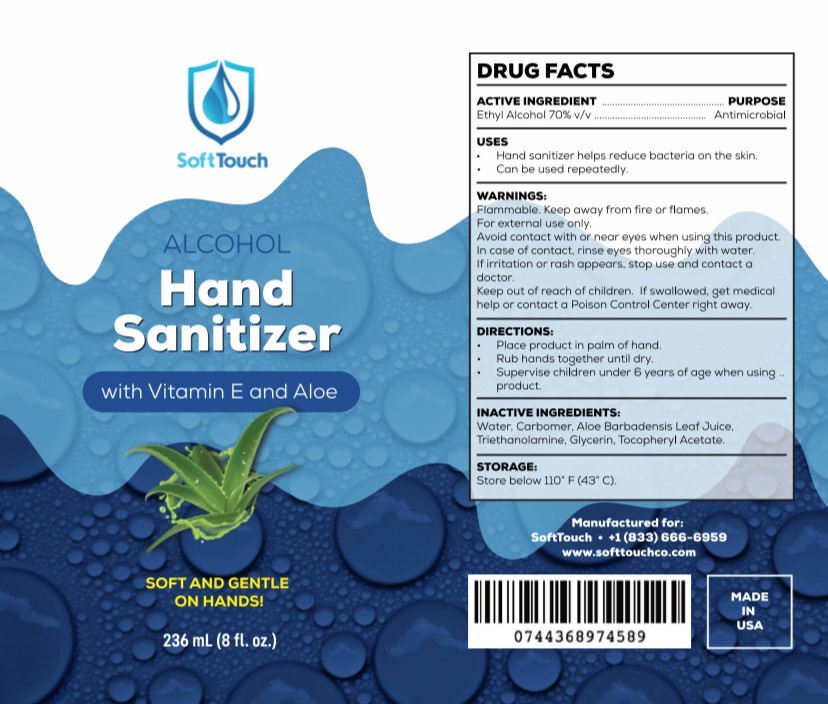 DRUG LABEL: SOFTTOUCH ALCOHOL HAND SANITIZER WITH VITAMIN E AND ALOE
NDC: 77699-101 | Form: GEL
Manufacturer: K&M COMMERCE INC
Category: otc | Type: HUMAN OTC DRUG LABEL
Date: 20200527

ACTIVE INGREDIENTS: ALCOHOL 70 mL/100 mL
INACTIVE INGREDIENTS: WATER; CARBOMER HOMOPOLYMER, UNSPECIFIED TYPE; ALOE VERA LEAF; TROLAMINE; GLYCERIN; .ALPHA.-TOCOPHEROL ACETATE

SOFTTOUCH ALCOHOL HAND SANITIZER WITH VITAMIN E AND ALOE

ACTIVE INGREDIENT

ETHYL ALCOHOL 70%

PURPOSE

ANTIMICROBIAL

USES

- HAND SANITIZER HELPS BACTERIA ON SKIN
- CAN BE USED REPEATEDLY

WARNINGS

FLAMMABLE, KEEP AWAY FROM FIRE OR FLAME.

FOR EXTERNAL USE ONLY: HANDS

AVOID CONTACT WITH OR NEAR EYES WHEN USING THIS PRODUCT.

IN CASE OF CONTACT, RINSE EYES THOROUGHLY WITH WATER.

IF IRRITATION OR RASH APPEARS, STOP USE AND CONTACT A DOCTOR.

KEEP OUT OF REACH OF CHILDREN. IF SWALLOWED, GET MEDICAL HELP OR CONTACT A POISON CONTROL CENTER RIGHT AWAY.

DIRECTIONS

- PLACE PRODUCT IN PALM OF HAND.
- RUB HANDS TOGETHER UNTIL DRY.
- SUPERVISE CHILDREN UNDER 6 YEARS OF AGE WHEN USING PRODUCT.

INACTIVE INGREDIENTS

WATER, CARBOPOL, ALOE BARBADENSIS LEAF JUICE, TRIETHANOLAMINE, GLYCERIN, TOCOPHERYL ACETATE